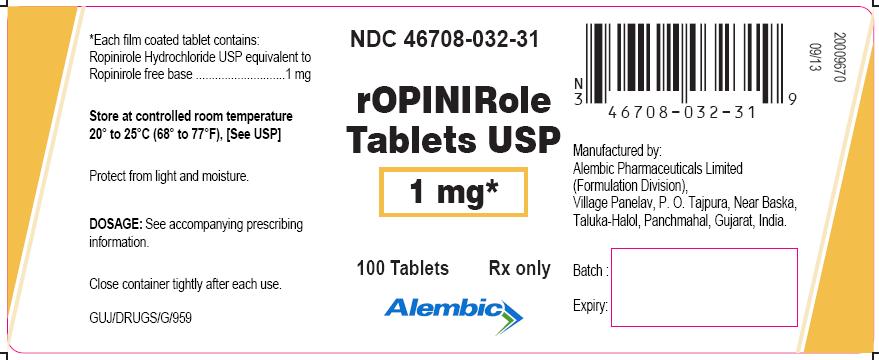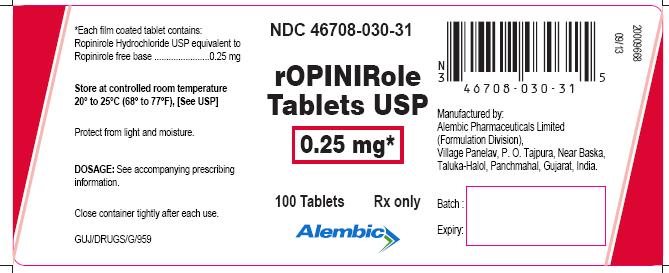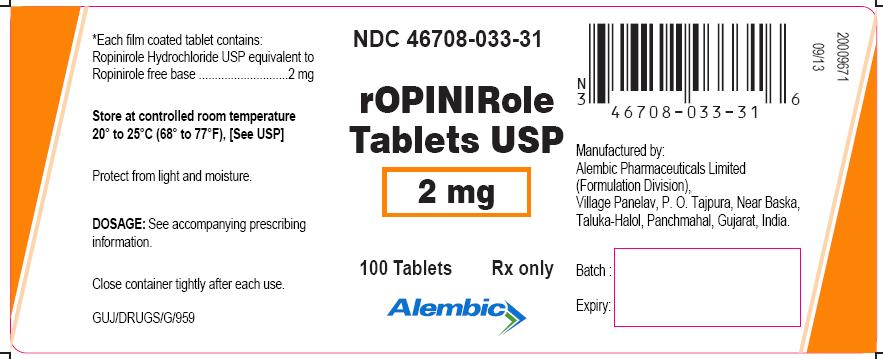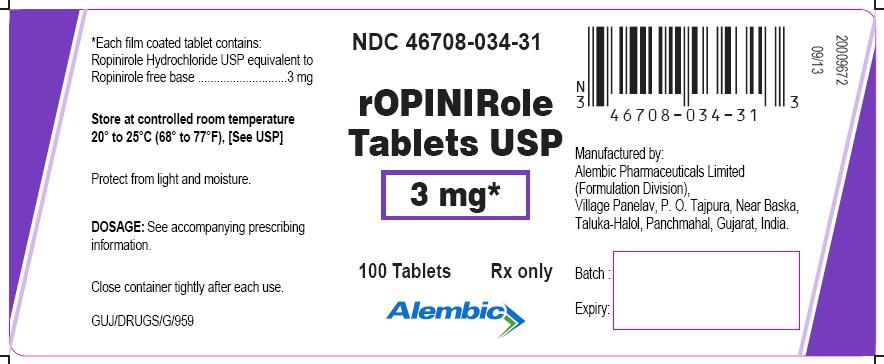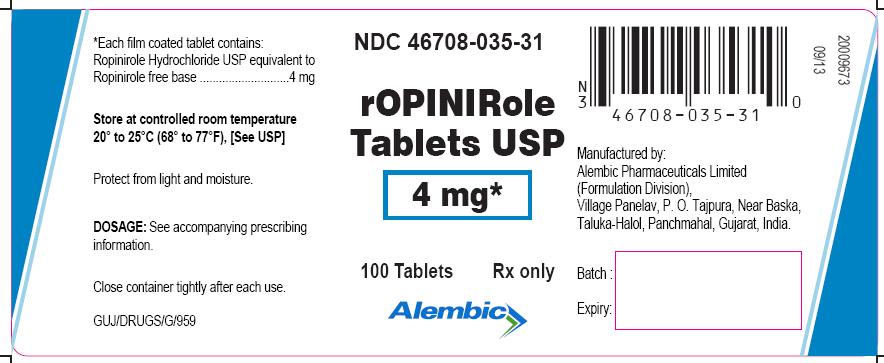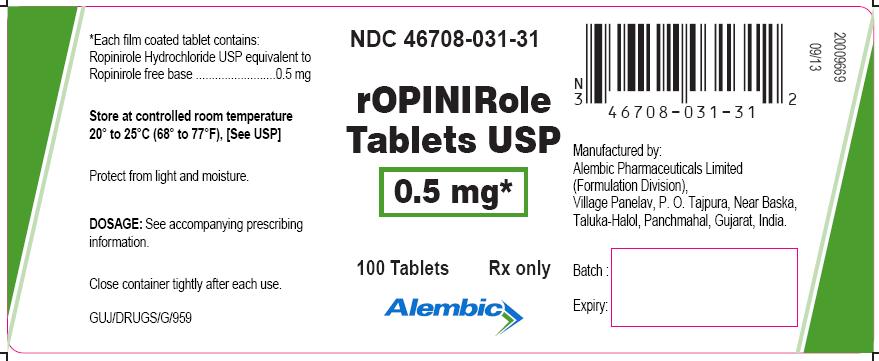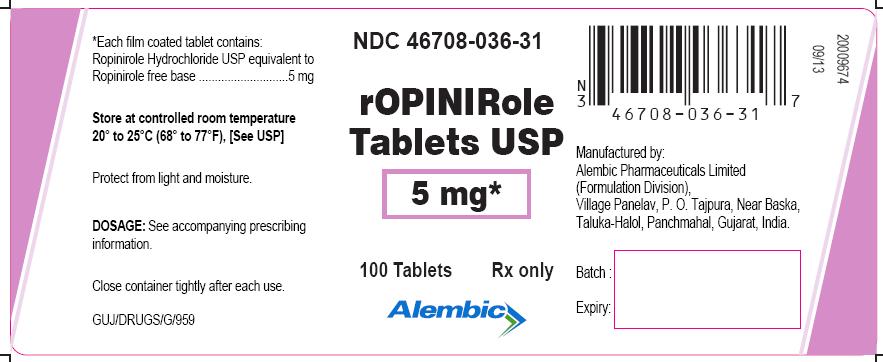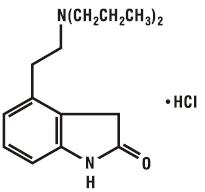 DRUG LABEL: ROPINIROLE
NDC: 46708-030 | Form: TABLET, FILM COATED
Manufacturer: Alembic Pharmaceuticals Limited
Category: prescription | Type: Human Prescription Drug Label
Date: 20250701

ACTIVE INGREDIENTS: ROPINIROLE HYDROCHLORIDE 0.25 mg/1 1
INACTIVE INGREDIENTS: CROSCARMELLOSE SODIUM; LACTOSE MONOHYDRATE; MAGNESIUM STEARATE; MICROCRYSTALLINE CELLULOSE; HYPROMELLOSE, UNSPECIFIED; POLYETHYLENE GLYCOL, UNSPECIFIED; POLYSORBATE 80; TITANIUM DIOXIDE

ROPINIROLE HYDROCHLORIDE - ropinirole hydrochloride tablet, film coated
Alembic Pharmaceuticals Limited

DESCRIPTION

Ropinirole is an orally administered non-ergoline dopamine agonist. It is the hydrochloride salt of 4-[2-(dipropylamino) ethyl]-1,3-dihydro-2H-indol-2-one monohydrochloride and has an empirical formula of C16H24N2O•HCl. The molecular weight is 296.84 (260.38 as the free base).
The structural formula is:

Ropinirole Hydrochloride, USP is a white to yellow solid with a melting range of 243° to 250°C and a solubility of 133 mg/mL in water.
Each circular, biconvex, film-coated tablet contains ropinirole hydrochloride USP equivalent to ropinirole free base, 0.25 mg, 0.5 mg, 1 mg, 2 mg, 3 mg, 4 mg, or 5 mg. Inactive ingredients consist of: croscarmellose sodium, lactose monohydrate, magnesium stearate, microcrystalline cellulose, and one or more of the following: carmine, FD&C Blue No. 2 aluminum lake, FD&C Yellow No. 6 aluminum lake, hypromellose, iron oxides (iron oxide yellow, iron oxide red and iron oxide black), polyethylene glycol, polysorbate 80 and titanium dioxide.

CLINICAL PHARMACOLOGY

Mechanism of Action
Ropinirole Hydrochloride is a non-ergoline dopamine agonist with high relative in vitro specificity and full intrinsic activity at the D2 and D3 dopamine receptor subtypes, binding with higher affinity to D3 than to D2 or D4 receptor subtypes.
Ropinirole has moderate in vitro affinity for opioid receptors. Ropinirole and its metabolites have negligible in vitro affinity for dopamine D1, 5-HT1, 5-HT2, benzodiazepine, GABA, muscarinic, alpha1-, alpha2-, and beta-adrenoreceptors.
Parkinson’s Disease
The precise mechanism of action of Ropinirole Hydrochloride as a treatment for Parkinson’s disease is unknown, although it is believed to be due to stimulation of postsynaptic dopamine D2-type receptors within the caudate-putamen in the brain. This conclusion is supported by studies that show that ropinirole improves motor function in various animal models of Parkinson’s disease. In particular, ropinirole attenuates the motor deficits induced by lesioning the ascending nigrostriatal dopaminergic pathway with the neurotoxin 1-methyl-4-phenyl-1,2,3,6-tetrahydropyridine (MPTP) in primates. The relevance of D3 receptor binding in Parkinson’s disease is unknown.
Restless Legs Syndrome (RLS)
The precise mechanism of action of Ropinirole Hydrochloride as a treatment for Restless Legs Syndrome (also known as Ekbom Syndrome) is unknown. Although the pathophysiology of RLS is largely unknown, neuropharmacological evidence suggests primary dopaminergic system involvement. Positron emission tomographic (PET) studies suggest that a mild striatal presynaptic dopaminergic dysfunction may be involved in the pathogenesis of RLS.
Clinical Pharmacology Studies
In healthy normotensive subjects, single oral doses of Ropinirole Tablets in the range 0.01 to 2.5 mg had little or no effect on supine blood pressure and pulse rates. Upon standing, Ropinirole Tablets caused decreases in systolic and diastolic blood pressure at doses above 0.25 mg. In some subjects, these changes were associated with the emergence of orthostatic symptoms, bradycardia, and, in one case, transient sinus arrest with syncope. With repeat dosing and slow titration up to 4 mg once daily in healthy volunteers, postural hypotension or hypotension-related adverse events were noted in 13% of subjects on Ropinirole Tablets and none of the subjects on placebo.
The mechanism of postural hypotension induced by Ropinirole Hydrochloride is presumed to be due to a D2-mediated blunting of the noradrenergic response to standing and subsequent decrease in peripheral vascular resistance. Nausea is a common concomitant symptom of orthostatic signs and symptoms.
At oral doses as low as 0.2 mg, Ropinirole Tablets suppressed serum prolactin concentrations in healthy male volunteers.
Ropinirole Tablets had no dose-related effect on ECG wave form and rhythm in young, healthy, male volunteers in the range of 0.01 to 2.5 mg.
Ropinirole Tablets had no dose- or exposure-related effect on mean QT intervals in healthy male and female volunteers titrated to doses up to 4 mg/day. The effect of Ropinirole Tablets on QT intervals at higher exposures achieved either due to drug interactions or at doses used in Parkinson’s disease has not been systematically evaluated.
Pharmacokinetics
Absorption, Distribution, Metabolism, and Elimination
The pharmacokinetics of ropinirole are similar in Parkinson's disease patients and patients with Restless Legs Syndrome. Ropinirole is rapidly absorbed after oral administration, reaching peak concentration in approximately 1-2 hours. In clinical studies, over 88% of a radiolabeled dose was recovered in urine and the absolute bioavailability was 55%, indicating a first-pass effect. Relative bioavailability from a tablet compared to an oral solution is 85%. Food does not affect the extent of absorption of ropinirole, although its Tmax is increased by 2.5 hours and its Cmaxis decreased by approximately 25% when the drug is taken with a high-fat meal. The clearance of ropinirole after oral administration to patients is 47 L/hr (cv = 45%) and its elimination half-life is approximately 6 hours. Ropinirole is extensively metabolized by the liver to inactive metabolites and displays linear kinetics over the therapeutic dosing range of 1 to 8 mg 3 times daily. Steady-state concentrations are expected to be achieved within 2 days of dosing. Accumulation upon multiple dosing is predictive from single dosing.
Ropinirole is widely distributed throughout the body, with an apparent volume of distribution of 7.5 L/kg (cv = 32%). It is up to 40% bound to plasma proteins and has a blood-to-plasma ratio of 1:1.
The major metabolic pathways are N-despropylation and hydroxylation to form the inactive N-despropyl and hydroxy metabolites. In vitro studies indicate that the major cytochrome P450 isozyme involved in the metabolism of ropinirole is CYP1A2, an enzyme known to be stimulated by smoking and omeprazole, and inhibited by, for example, fluvoxamine, mexiletine, and the older fluoroquinolones such as ciprofloxacin and norfloxacin. The N-despropyl metabolite is converted to carbamyl glucuronide, carboxylic acid, and N-despropyl hydroxy metabolites. The hydroxy metabolite of ropinirole is rapidly glucuronidated. Less than 10% of the administered dose is excreted as unchanged drug in urine. N-despropyl ropinirole is the predominant metabolite found in urine (40%), followed by the carboxylic acid metabolite (10%), and the glucuronide of the hydroxy metabolite (10%).
P450 Interaction
In vitro metabolism studies showed that CYP1A2 was the major enzyme responsible for the metabolism of ropinirole. Inhibitors or inducers of this enzyme have been shown to alter its clearance when coadministered with ropinirole. Therefore, if therapy with a drug known to be a potent inhibitor of CYP1A2 is stopped or started during treatment with Ropinirole Tablets, adjustment of the dose of Ropinirole Tablets may be required.
Population Subgroups
Because therapy with Ropinirole Tablets is initiated at a low dose and gradually titrated upward according to clinical tolerability to obtain the optimum therapeutic effect, adjustment of the initial dose based on gender, weight, or age is not necessary.
Age
Oral clearance of ropinirole is reduced by 30% in patients above 65 years of age compared to younger patients. Dosage adjustment is not necessary in the elderly (above 65 years), as the dose of ropinirole is to be individually titrated to clinical response.
Gender
Female and male patients showed similar oral clearance.
Race
The influence of race on the pharmacokinetics of ropinirole has not been evaluated.
Cigarette Smoking
Smoking is expected to increase the clearance of ropinirole since CYP1A2 is known to be induced by smoking. In a study in patients with RLS, smokers (n = 7) had an approximate 30% lower Cmaxand a 38% lower AUC than did nonsmokers (n = 11), when those parameters were normalized for dose.
Renal Impairment
Based on population pharmacokinetic analysis, no difference was observed in the pharmacokinetics of ropinirole in patients with moderate renal impairment (creatinine clearance between 30 to 50 mL/min.) compared to an age-matched population with creatinine clearance above 50 mL/min. Therefore, no dosage adjustment is necessary in moderately renally impaired patients. The use of Ropinirole Tablets in patients with severe renal impairment has not been studied.
The effect of hemodialysis on drug removal is not known, but because of the relatively high apparent volume of distribution of ropinirole (525 L), the removal of the drug by hemodialysis is unlikely.
Hepatic Impairment
The pharmacokinetics of ropinirole have not been studied in hepatically impaired patients. These patients may have higher plasma levels and lower clearance of the drug than patients with normal hepatic function. The drug should be titrated with caution in this population.
Other Diseases
Population pharmacokinetic analysis revealed no change in the oral clearance of ropinirole in patients with concomitant diseases such as hypertension, depression, osteoporosis/arthritis, and insomnia compared to patients with Parkinson’s disease only.
Clinical Trials
Parkinson's Disease
The effectiveness of Ropinirole Tablets in the treatment of Parkinson’s disease was evaluated in a multinational drug development program consisting of 11 randomized, controlled trials. Four were conducted in patients with early Parkinson’s disease and no concomitant levodopa (L-dopa), and 7 were conducted in patients with advanced Parkinson’s disease with concomitant L-dopa.
Among these 11 studies, 3 placebo-controlled studies provide the most persuasive evidence of ropinirole’s effectiveness in the management of patients with Parkinson’s disease who were and were not receiving concomitant L-dopa. Two of these 3 trials enrolled patients with early Parkinson’s disease (without L-dopa) and 1 enrolled patients receiving L-dopa.
In these studies a variety of measures were used to assess the effects of treatment (e.g., the Unified Parkinson’s Disease Rating Scale [UPDRS], Clinical Global Impression [CGI] scores, patient diaries recording time “on” and “off,” and tolerability of L-dopa dose reductions).
In both studies of early Parkinson’s disease (without L-dopa) patients, the motor component (Part III) of the UPDRS was the primary outcome assessment. The UPDRS is a 4-part multi-item rating scale intended to evaluate mentation (Part I), activities of daily living (Part II), motor performance (Part III), and complications of therapy (Part IV). Part III of the UPDRS contains 14 items designed to assess the severity of the cardinal motor findings in patients with Parkinson’s disease (e.g., tremor, rigidity, bradykinesia, postural instability, etc.) scored for different body regions and has a maximum (worst) score of 108. Responders were defined as patients with at least a 30% reduction in the Part III score.
In the study of advanced Parkinson’s disease (with L-dopa) patients, both reduction in percent awake time spent“off” and the ability to reduce the daily use of L-dopa were assessed as a combined endpoint and individually.
Studies in Patients With Early Parkinson’s Disease (Without L-dopa)
One early therapy study was a 12-week multicenter study in which 63 patients (41 on Ropinirole Tablets) with idiopathic Parkinson’s disease receiving concomitant anti-Parkinson medication (but not L-dopa) were randomized to either Ropinirole Tablets or placebo. Patients had a mean disease duration of approximately 2 years. Patients were eligible for enrollment if they presented with bradykinesia and at least tremor, rigidity, or postural instability. In addition, they must have been classified as Hoehn & Yahr Stage I-IV. This scale, ranging from I = unilateral involvement with minimal impairment to V = confined to wheelchair or bed, is a standard instrument used for staging patients with Parkinson’s disease. The primary outcome measure in this trial was the proportion of patients experiencing a decrease (compared to baseline) of at least 30% in the UPDRS motor score.
Patients were titrated for up to 10 weeks, starting at 0.5 mg twice daily, with weekly increments of 0.5 mg twice daily to a maximum of 5 mg twice daily. Once patients reached their maximally tolerated dose (or 5 mg twice daily), they were maintained on that dose through 12 weeks. The mean dose achieved by patients at study endpoint was 7.4 mg/day. At the end of 12 weeks, 71% of patients treated with Ropinirole Tablets were responders, compared with 41% of patients in the placebo group (p = 0.021).
Statistically significant differences between the percentage of responders on Ropinirole Tablets compared to placebo were seen after 8 weeks of treatment.
In addition, the mean percentage improvement from baseline in the Total Motor Score was 43% in patients treated with Ropinirole Tablets compared with 21% in patients treated with placebo (p = 0.018).
Statistically significant differences in UPDRS motor score between Ropinirole Tablets and placebo were seen after 2 weeks of treatment.
The median daily dose at which a 30% reduction in UPDRS motor score was sustained was 4 mg.
The second trial in early Parkinson’s disease (without L-dopa) patients was a double-blind, randomized, placebo-controlled, 6-month study. Patients were essentially similar to those in the study described above; concomitant use of selegiline was allowed, but patients were not permitted to use anticholinergics or amantadine during the study. Patients had a mean disease duration of 2 years and limited (not more than a 6-week period) or no prior exposure to L-dopa. The starting dose of Ropinirole Tablets in this trial was 0.25 mg 3 times daily. The dose was titrated at weekly intervals by increments of 0.25 mg 3 times daily to a dose of 1 mg 3 times daily. Further titrations at weekly intervals were at increments of 0.5 mg 3 times daily up to a dose of 3 mg 3 times daily, and then weekly at increments of 1 mg 3 times daily. Patients were to be titrated to a dose of at least 1.5 mg 3 times daily and then to their maximally tolerated dose, up to a maximum of 8 mg 3 times daily. The mean dose attained in patients at study endpoint was 15.7 mg/day.
The primary measure of effectiveness was the mean percent reduction (improvement) from baseline in the UPDRS Motor Score. In this study 241 patients were enrolled. At the end of the 6-month study, patients treated with Ropinirole Tablets had 22% improvement in motor score, compared with a 4% worsening in the placebo group (p<0.001).
Statistically significant differences in UPDRS motor score improvement between Ropinirole Tablets and placebo were seen after 12 weeks of treatment.
Study in Patients With Advanced Parkinson’s Disease (With L-dopa)
This double-blind, randomized, placebo-controlled, 6-month trial evaluated 148 patients (Hoehn & Yahr II-IV) who were not adequately controlled on L-dopa. Patients in this study had a mean disease duration of approximately 9 years, had been exposed to L-dopa for approximately 7 years, and had experienced “on-off” periods with L-dopa therapy. Patients previously receiving stable doses of selegiline, amantadine, and/or anticholinergic agents could continue on these agents during the study. Patients were started at a dose of 0.25 mg 3 times daily of Ropinirole Tablets and titrated upward by weekly intervals until an optimal therapeutic response was achieved. The maximum dose of study medication was 8 mg 3 times daily. All patients had to be titrated to at least a dose of 2.5 mg 3 times daily. Patients could then be maintained on this dose level or higher for the remainder of the study. Once a dose of 2.5 mg 3 times daily was achieved, patients underwent a mandatory reduction in their L-dopa dose, to be followed by additional mandatory reductions with continued escalation of the dose of Ropinirole Tablets. Reductions in the dosage of L-dopa were also allowed if patients experienced adverse events that the investigator considered related to dopaminergic therapy. The mean dose attained at study endpoint was 16.3 mg/day. The primary outcome was the proportion of responders, defined as patients who were able both to achieve a decrease (compared to baseline) of at least 20% in their L-dopa dose and a decrease of at least 20% in the proportion of the time awake in the “off” condition (a period of time during the day when patients are particularly immobile), as determined by patient diary. In addition, the mean percent change from baseline in daily L-dopa dose was examined.
At the end of 6 months, 28% of patients treated with Ropinirole Tablets were classified as responders (based on combined endpoint) while 11% of patients treated with placebo were responders (p = 0.02). Based on the protocol-mandated reductions in L-dopa dosage with escalating doses of Ropinirole Tablets, patients treated with Ropinirole Tablets had a 19.4% mean reduction in L-dopa dose while patients treated with placebo had a 3% reduction (p<0.001). L-dopa dosage reduction was also allowed during the study if dyskinesias or other dopaminergic effects occurred. Overall, reduction of L-dopa dose was sustained in 87% of patients treated with Ropinirole Tablets and in 57% of patients on placebo. On average, the L-dopa dose was reduced by 31% in patients treated with Ropinirole Tablets.
The mean number of “off” hours per day during baseline was 6.4 hours for patients treated with Ropinirole Tablets and 7.3 hours for patients treated with placebo. At the end of the 6-month study, patients treated with Ropinirole Tablets had a mean of 4.9 hours per day of “off” time, while placebo-treated patients had a mean of 6.4 hours per day of “off” time.
Restless Legs Syndrome (RLS)
The effectiveness of Ropinirole Tablets in the treatment of RLS was demonstrated in randomized, double-blind, placebo-controlled studies in adults diagnosed with RLS using the International Restless Legs Syndrome Study Group diagnostic criteria (see INDICATIONS AND USAGE). Patients were required to have a history of a minimum of 15 RLS episodes/month during the previous month and a total score of ≥15 on the International RLS Rating Scale (IRLS scale) at baseline. Patients with RLS secondary to other conditions (e.g., pregnancy, renal failure, and anemia) were excluded. All studies employed flexible dosing, with patients initiating therapy at 0.25 mg Ropinirole Tablets once daily. Patients were titrated based on clinical response and tolerability over 7 weeks to a maximum of 4 mg once daily. All doses were taken between 1 and 3 hours before bedtime.
A variety of measures were used to assess the effects of treatment, including the IRLS Scale and Clinical Global Impression-Global Improvement (CGI-I) scores. The IRLS Scale contains 10 items designed to assess the severity of sensory and motor symptoms, sleep disturbance, daytime somnolence, and impact on activities of daily living and mood associated with RLS. The range of scores is 0 to 40, with 0 being absence of RLS symptoms and 40 the most severe symptoms. Three of the controlled studies utilized the change from baseline in the IRLS Scale at the week 12 endpoint as the primary efficacy outcome.
Three hundred eighty patients were randomized to receive Ropinirole Tablets (n = 187) or placebo (n = 193) in a US study; 284 were randomized to receive either Ropinirole Tablets (n = 146) or placebo (n = 138) in a multinational study (excluding US); and 267 patients were randomized to Ropinirole Tablets (n = 131) or placebo (n = 136) in a multinational study (including US). Across the 3 studies, the mean duration of RLS was 16 to 22 years (range of 0 to 65 years), mean age was approximately 54 years (range of 18 to 79 years), and approximately 61% were women. The mean dose at week 12 was approximately 2 mg/day for the 3 studies.
In all 3 studies, a statistically significant difference between the treatment group receiving Ropinirole Tablets and the treatment group receiving placebo was observed at week 12 for both the mean change from baseline in the IRLS Scale total score and the percentage of patients rated as responders (much improved or very much improved) on the CGI-I (see Table 1).
Table 1. Mean Change in IRLS Score and Percent Responders on CGI-I

 | Ropinirole Tablets | Placebo | p-value
Mean Change in IRLS score at Week 12
US study | -13.5 | -9.8 | p<0.0001
Multinational study (excluding US) | -11.0 | -8.0 | p=0.0036
Multinational study (including US) | -11.2 | -8.7 | p=0.0197
Percent responders on CGI-I at Week 12
US study | 73.3% | 56.5% | p=0.0006
Multinational study (excluding US) | 53.4% | 40.9% | p=0.0416
Multinational study (including US) | 59.5% | 39.6% | p=0.0010

Long-term maintenance of efficacy in the treatment of RLS was demonstrated in a 36-week study. Following a 24-week single-blind treatment phase (flexible doses of Ropinirole Tablets of 0.25 to 4 mg once daily), patients who were responders (defined as a decrease of >6 points on the IRLS Scale total score relative to baseline) were randomized in double-blind fashion to placebo or continuation of Ropinirole Tablets for an additional 12 weeks. Relapse was defined as an increase of at least 6 points on the IRLS Scale total score to a total score of at least 15, or withdrawal due to lack of efficacy. For patients who were responders at week 24, the mean dose of ropinirole was 2 mg (range 0.25 to 4 mg).Patients continued on Ropinirole Tablets demonstrated a significantly lower relapse rate compared with patients randomized to placebo (32.6% vs 57.8%, p = 0.0156).

INDICATIONS & USAGE

Parkinson’s Disease
Ropinirole Tablets are indicated for the treatment of the signs and symptoms of idiopathic Parkinson’s disease.
The effectiveness of Ropinirole Tablets were demonstrated in randomized, controlled trials in patients with early Parkinson’s disease who were not receiving concomitant L-dopa therapy as well as in patients with advanced disease on concomitant L-dopa (see CLINICAL PHARMACOLOGY: Clinical Trials).
Restless Legs Syndrome
Ropinirole Tablets are indicated for the treatment of moderate-to-severe primary Restless Legs Syndrome (RLS).
Key diagnostic criteria for RLS are: an urge to move the legs usually accompanied or caused by uncomfortable and unpleasant leg sensations; symptoms begin or worsen during periods of rest or inactivity such as lying or sitting; symptoms are partially or totally relieved by movement such as walking or stretching at least as long as the activity continues; and symptoms are worse or occur only in the evening or night. Difficulty falling asleep may frequently be associated with moderate-to-severe RLS.

CONTRAINDICATIONS

Ropinirole Tablets are contraindicated for patients known to have hypersensitivity to the product.

WARNINGS

Falling Asleep During Activities of Daily Living

Patients treated with Ropinirole Tablets have reported falling asleep while engaged in activities of daily living, including the operation of motor vehicles, which sometimes resulted in accidents. Although many of these patients reported somnolence while on Ropinirole Tablets, some perceived that they had no warning signs such as excessive drowsiness, and believed that they were alert immediately prior to the event. Some of these events have been reported as late as 1 year after initiation of treatment.

In controlled clinical trials, somnolence was a common occurrence in patients receiving Ropinirole Tablets and is more frequent in Parkinson's disease (up to 40% Ropinirole Tablets, 6% placebo) than in Restless Legs Syndrome (12% Ropinirole Tablets, 6% placebo). Many clinical experts believe that falling asleep while engaged in activities of daily living always occurs in a setting of preexisting somnolence, although patients may not give such a history. For this reason, prescribers should continually reassess patients for drowsiness or sleepiness, especially since some of the events occur well after the start of treatment. Prescribers should also be aware that patients may not acknowledge drowsiness or sleepiness until directly questioned about drowsiness or sleepiness during specific activities.

Before initiating treatment with Ropinirole Tablets, patients should be advised of the potential to develop drowsiness and specifically asked about factors that may increase the risk with Ropinirole Tablets such as concomitant sedating medications, the presence of sleep disorders (other than Restless Legs Syndrome), and concomitant medications that increase ropinirole plasma levels (e.g., ciprofloxacin - see PRECAUTIONS: Drug Interactions). If a patient develops significant daytime sleepiness or episodes of falling asleep during activities that require active participation (e.g., conversations, eating, etc.), Ropinirole Tablets should ordinarily be discontinued. (See DOSAGE AND ADMINISTRATION for guidance in discontinuing Ropinirole Tablets.) If a decision is made to continue Ropinirole Tablets, patients should be advised to not drive and to avoid other potentially dangerous activities. There is insufficient information to establish that dose reduction will eliminate episodes of falling asleep while engaged in activities of daily living.
Syncope

Syncope, sometimes associated with bradycardia, was observed in association with ropinirole in both Parkinson’s disease patients and RLS patients. In the 2 double-blind, placebo-controlled studies of Ropinirole Tablets in patients with Parkinson’s disease who were not being treated with L-dopa, 11.5% (18 of 157) of patients on Ropinirole Tablets had syncope compared to 1.4% (2 of 147) of patients on placebo. Most of these cases occurred more than 4 weeks after initiation of therapy with Ropinirole Tablets, and were usually associated with a recent increase in dose.

Of 208 patients being treated with both L-dopa and Ropinirole Tablets in placebo-controlled advanced Parkinson’s disease trials, there were reports of syncope in 6 (2.9%) compared to 2 of 120 (1.7%) of placebo/L-dopa patients.

In patients with RLS, of 496 patients treated with Ropinirole Tablets in 12-week placebo-controlled trials, there were reports of syncope in 5 (1.0%) compared with 1 of 500 (0.2%) patients treated with placebo.

Because the studies of Ropinirole Tablets excluded patients with significant cardiovascular disease, it is not known to what extent the estimated incidence figures apply to either Parkinson’s disease or RLS patients in clinical practice. Therefore, patients with severe cardiovascular disease should be treated with caution.

Two of 47 Parkinson’s disease patient volunteers enrolled in phase 1 studies had syncope following a 1-mg dose. In 2 studies in RLS patients that used a forced titration regimen and orthostatic challenge with intensive blood pressure monitoring, 1 of 55 RLS patients treated with Ropinirole Tablets compared with 0 of 27 patients receiving placebo reported syncope. In phase 1 studies including 110 healthy volunteers, 1 patient developed hypotension, bradycardia, and sinus arrest of 26 seconds accompanied by syncope; the patient recovered spontaneously without intervention. One other healthy volunteer reported syncope.
Symptomatic Hypotension

Dopamine agonists, in clinical studies and clinical experience, appear to impair the systemic regulation of blood pressure, with resulting postural hypotension, especially during dose escalation. Parkinson’s disease patients, in addition, appear to have an impaired capacity to respond to a postural challenge. For these reasons, Parkinson’s patients being treated with dopaminergic agonists ordinarily (1) require careful monitoring for signs and symptoms of postural hypotension, especially during dose escalation, and (2) should be informed of this risk (see PRECAUTIONS: Information for Patients).

Although the clinical trials were not designed to systematically monitor blood pressure, there were individual reported cases of postural hypotension in early Parkinson’s disease (without L-dopa) in patients treated with Ropinirole Tablets. Most of these cases occurred more than 4 weeks after initiation of therapy with Ropinirole Tablets and were usually associated with a recent increase in dose.

In 12-week placebo-controlled trials of patients with RLS, the adverse event orthostatic hypotension was reported by 4 of 496 patients (0.8%) treated with Ropinirole Tablets compared with 2 of 500 patients (0.4%) receiving placebo.

In two phase 2 studies in patients with RLS that used a forced-titration regimen and orthostatic challenges with intensive blood pressure monitoring, 14 of 55 patients (25%) receiving Ropinirole Tablets experienced an adverse event of hypotension or postural hypotension. As described above, one additional patient was noted to have an episode of vasovagal syncope (although no blood pressure recording was documented). None of the 27 patients receiving placebo had a similar adverse event. In these studies, 11 of the 55 patients (20%) receiving Ropinirole Tablets and 3 of the 26 patients (12%) who had post-dose blood pressure assessments following placebo, experienced an orthostatic blood pressure decrease of at least 40 mm Hg systolic and/or at least 20 mm Hg diastolic; not all of these changes were associated with clinical symptoms. Except for its forced nature these studies used a similar titration schedule as those in the phase 3 efficacy trials.

In phase 1 studies of Ropinirole Tablets that included 110 healthy volunteers, 9 subjects had documented symptomatic postural hypotension. These episodes appeared mainly at doses above 0.8 mg and these doses are higher than the starting doses recommended for either Parkinson’s disease patients or RLS patients. In 8 of these 9 individuals, the hypotension was accompanied by bradycardia, but did not develop into syncope (see Syncope subsection). None of these events resulted in death or hospitalization.

One of 47 Parkinson’s disease patient volunteers enrolled in phase 1 studies had documented hypotension following a 2-mg dose on 2 occasions.
Hallucinations
In double-blind, placebo-controlled, early-therapy studies in patients with Parkinson’s disease who were not treated with L-dopa, 5.2% (8 of 157) of patients treated with Ropinirole Tablets reported hallucinations, compared to 1.4% of patients on placebo (2 of 147). Among those patients receiving both Ropinirole Tablets and L-dopa in advanced Parkinson’s disease (with L-dopa) studies, 10.1% (21 of 208) were reported to experience hallucinations, compared to 4.2% (5 of 120) of patients treated with placebo and L-dopa.
Hallucinations were of sufficient severity to cause discontinuation of treatment in 1.3% of the early Parkinson’s disease (without L-dopa) patients and 1.9% of the advanced Parkinson’s disease (with L-dopa) patients, compared to 0% and 1.7% of placebo patients, respectively.
In patients with RLS, hallucinations were reported by 0% of patients treated with Ropinirole Tablets (0 of 496) compared with 0.2% of patients who received placebo (1 of 500) in the 12-week placebo-controlled trials; in premarketing long-term open-label studies, 0.5% of patients reported hallucinations during therapy with Ropinirole Tablets (2 of 390) but did not discontinue treatment and symptoms resolved.

PRECAUTIONS

GENERAL

Dyskinesia
Ropinirole Tablets may potentiate the dopaminergic side effects of L-dopa and may cause and/or exacerbate preexisting dyskinesia in patients treated with L-dopa for Parkinson's disease. Decreasing the dose of L-dopa may ameliorate this side effect.
Renal Impairment
No dosage adjustment is needed in patients with mild to moderate renal impairment (creatinine clearance of 30 to 50 mL/min). The use of Ropinirole Tablets in patients with severe renal impairment has not been studied.
Hepatic Impairment
The pharmacokinetics of ropinirole have not been studied in patients with hepatic impairment. Since patients with hepatic impairment may have higher plasma levels and lower clearance, Ropinirole Tablets should be titrated with caution in these patients.
Events Reported With Dopaminergic Therapy
Withdrawal-Emergent Hyperpyrexia and Confusion
Although not reported with Ropinirole Tablets, a symptom complex resembling the neuroleptic malignant syndrome (characterized by elevated temperature, muscular rigidity, altered consciousness, and autonomic instability), with no other obvious etiology, has been reported in association with rapid dose reduction, withdrawal of, or changes in anti-Parkinsonian therapy.
Fibrotic Complications
Cases of retroperitoneal fibrosis, pulmonary infiltrates, pleural effusion, pleural thickening, pericarditis, and cardiac valvulopathy have been reported in some patients treated with ergot-derived dopaminergic agents. While these complications may resolve when the drug is discontinued, complete resolution does not always occur.
Although these adverse events are believed to be related to the ergoline structure of these compounds, whether other, nonergot-derived dopamine agonists can cause them is unknown.
A small number of reports have been received of possible fibrotic complications, including pleural effusion, pleural fibrosis, interstitial lung disease, and cardiac valvulopathy, in the development program and postmarketing experience for Ropinirole Tablets. While the evidence is not sufficient to establish a causal relationship between Ropinirole Tablets and these fibrotic complications, a contribution of Ropinirole Tablets cannot be completely ruled out in rare cases.
Melanoma
Epidemiologic studies have shown that patients with Parkinson’s disease have a higher risk (2- to approximately 6-fold higher) of developing melanoma than the general population. Whether the increased risk observed was due to Parkinson’s disease or other factors, such as drugs used to treat Parkinson’s disease, is unclear.
For the reasons stated above, patients and providers are advised to monitor for melanomas frequently and on a regular basis when using Ropinirole Tablets for any indication. Ideally, periodic skin examinations should be performed by appropriately qualified individuals (e.g., dermatologists).
Augmentation and Rebound in RLS
Reports in the literature indicate treatment of RLS with dopaminergic medications can result in a worsening of symptoms in the early morning hours, referred to as rebound. Augmentation has also been described during therapy for RLS. Augmentation refers to the earlier onset of symptoms in the evening (or even the afternoon), increase in symptoms, and spread of symptoms to involve other extremities. The controlled trials of Ropinirole Tablets in patients with RLS excluded patients with augmentation and rebound and were generally not of sufficient duration to capture these phenomena. The frequency of augmentation and/or rebound after longer use of Ropinirole Tablets and the appropriate management of these events, have not been evaluated in controlled clinical trials.
Retinal Pathology
Albino Rats
Retinal degeneration was observed in albino rats in the 2-year carcinogenicity study at all doses tested (equivalent to 0.6 to 20 times the maximum recommended human dose on a mg/m2 basis), but was statistically significant at the highest dose (50 mg/kg/day). Additional studies to further evaluate the specific pathology (e.g., loss of photoreceptor cells) have not been performed. Similar changes were not observed in a 2-year carcinogenicity study in albino mice or in rats or monkeys treated for 1 year. The potential significance of this effect in humans has not been established, but cannot be disregarded because disruption of a mechanism that is universally present in vertebrates (e.g., disk shedding) may be involved.
Human
In order to evaluate the effect of Ropinirole Tablets in humans, ocular electroretinogram (ERG) assessments were conducted during a 2-year, double-blind, multicenter, flexible dose, L-dopa controlled clinical study of Ropinirole Tablets in patients with Parkinson's disease. A total of 156 patients (78 on ropinirole, mean dose 11.9 mg/day and 78 on L-dopa, mean dose 555.2 mg/day) were evaluated for evidence of retinal dysfunction through electroretinograms. There was no clinically meaningful difference between the treatment groups in retinal function over the duration of the study.
Binding to Melanin
Ropinirole Hydrochloride binds to melanin-containing tissues (i.e., eyes, skin) in pigmented rats. After a single dose, long-term retention of drug was demonstrated, with a half-life in the eye of 20 days. It is not known if Ropinirole Hydrochloride accumulates in these tissues over time.

INFORMATION FOR PATIENTS

Physicians should instruct their patients to read the Patient Information leaflet before starting therapy with Ropinirole Tablets and to reread it upon prescription renewal for new information regarding the use of Ropinirole Tablets.
Patients should be instructed to take Ropinirole Tablets only as prescribed. If a dose is missed, patients should be advised not to double their next dose.
Ropinirole Tablets can be taken with or without food. Patients may be advised that taking Ropinirole Tablets with food may reduce the occurrence of nausea. However, this has not been established in controlled clinical trials.
Patients should be advised that they may develop postural (orthostatic) hypotension with or without symptoms such as dizziness, nausea, syncope, and sometimes sweating. Hypotension and/or orthostatic symptoms may occur more frequently during initial therapy or with an increase in dose at any time (cases have been seen after weeks of treatment). Accordingly, patients should be cautioned against rising rapidly after sitting or lying down, especially if they have been doing so for prolonged periods, and especially at the initiation of treatment with Ropinirole Tablets.
Patients should be alerted to the potential sedating effects associated with Ropinirole Tablets, including somnolence and the possibility of falling asleep while engaged in activities of daily living. Since somnolence is a frequent adverse event with potentially serious consequences, patients should neither drive a car nor engage in other potentially dangerous activities until they have gained sufficient experience with Ropinirole Tablets to gauge whether or not it affects their mental and/or motor performance adversely. Patients should be advised that if increased somnolence or episodes of falling asleep during activities of daily living (e.g., watching television, passenger in a car, etc.) are experienced at any time during treatment, they should not drive or participate in potentially dangerous activities until they have contacted their physician.
Because of possible additive effects, caution should be advised when patients are taking other sedating medications or alcohol in combination with Ropinirole Tablets and when taking concomitant medications that increase plasma levels of ropinirole (e.g., ciprofloxacin).
Because of the possible additive sedative effects, caution should also be used when patients are taking alcohol or other CNS depressants (e.g., benzodiazepines, antipsychotics, antidepressants, etc.) in combination with Ropinirole Tablets.
Patients should be informed they may experience hallucinations (unreal visions, sounds, or sensations) while taking Ropinirole Tablets. These were uncommon in patients taking Ropinirole Tablets for Restless Legs Syndrome. The risk is greater in patients with Parkinson's disease; the elderly are at greater risk than younger patients with Parkinson's disease; and the risk is greater in patients who are taking Ropinirole Tablets with L-dopa, or taking higher doses of Ropinirole Tablets.
Impulse Control Symptoms Including Compulsive Behaviors:There have been reports of patients experiencing intense urges to gamble, increased sexual urges, and other intense urges and the inability to control these urges while taking one or more of the medications that increase central dopaminergic tone, that are generally used for the treatment of Parkinson’s disease, including Ropinirole Tablets. Although it is not proven that the medications caused these events, these urges were reported to have stopped in some cases when the dose was reduced or the medication was stopped. Prescribers should ask patients about the development of new or increased gambling urges, sexual urges or other urges while being treated with Ropinirole Tablets. Patients should inform their physician if they experience new or increased gambling urges, increased sexual urges or other intense urges while taking Ropinirole Tablets. Physicians should consider dose reduction or stopping the medication if a patient develops such urges while taking Ropinirole Tablets.
Because of the possibility that ropinirole may be excreted in breast milk, patients should be advised to notify their physicians if they intend to breastfeed or are breastfeeding an infant.
Because ropinirole has been shown to have adverse effects on embryo-fetal development, including teratogenic effects, in animals, and because experience in humans is limited, patients should be advised to notify their physician if they become pregnant or intend to become pregnant during therapy (see PRECAUTIONS: Pregnancy).

DRUG INTERACTIONS

P450 Interaction
In vitro metabolism studies showed that CYP1A2 was the major enzyme responsible for the metabolism of ropinirole. There is thus the potential for substrates or inhibitors of this enzyme when coadministered with ropinirole to alter its clearance. Therefore, if therapy with a drug known to be a potent inhibitor of CYP1A2 is stopped or started during treatment with Ropinirole Tablets, adjustment of the dose of Ropinirole Tablets may be required.
L-dopa
Co-administration of carbidopa + L-dopa (SINEMET® 10/100 mg twice daily) with ropinirole (2 mg 3 times daily) had no effect on the steady-state pharmacokinetics of ropinirole (n = 28 patients). Oral administration of Ropinirole Tablets 2 mg 3 times daily increased mean steady state Cmax of L-dopa by 20%, but its AUC was unaffected (n = 23 patients).
Digoxin
Co-administration of Ropinirole Tablets (2 mg 3 times daily) with digoxin (0.125 to 0.25 mg once daily) did not alter the steady-state pharmacokinetics of digoxin in 10 patients.
Theophylline
Administration of theophylline (300 mg twice daily, a substrate of CYP1A2) did not alter the steady-state pharmacokinetics of ropinirole (2 mg 3 times daily) in 12 patients with Parkinson’s disease. Ropinirole (2 mg 3 times daily) did not alter the pharmacokinetics of theophylline (5 mg/kg IV) in 12 patients with Parkinson’s disease.
Ciprofloxacin
Co-administration of ciprofloxacin (500 mg twice daily), an inhibitor of CYP1A2, with ropinirole (2 mg 3 times daily) increased ropinirole AUC by 84% on average and Cmax by 60% (n = 12 patients).
Estrogens
Population pharmacokinetic analysis revealed that estrogens (mainly ethinyl estradiol: intake 0.6 to 3 mg over 4-month to 23-year period) reduced the oral clearance of ropinirole by 36% in 16 patients. Dosage adjustment may not be needed for Ropinirole Tablets in patients on estrogen therapy because patients must be carefully titrated with ropinirole to tolerance or adequate effect. However, if estrogen therapy is stopped or started during treatment with Ropinirole Tablets, then adjustment of the dose of Ropinirole Tablets may be required.
Dopamine Antagonists
Since ropinirole is a dopamine agonist, it is possible that dopamine antagonists such as neuroleptics (phenothiazines, butyrophenones, thioxanthenes) or metoclopramide may diminish the effectiveness of Ropinirole Tablets. Patients with major psychotic disorders treated with neuroleptics should only be treated with dopamine agonists if the potential benefits outweigh the risks.
Population analysis showed that commonly administered drugs, e.g., selegiline, amantadine, tricyclic antidepressants, benzodiazepines, ibuprofen, thiazides, antihistamines, and anticholinergics, did not affect the oral clearance of ropinirole.

CARCINOGENESIS & MUTAGENESIS & IMPAIRMENT OF FERTILITY

Two-year carcinogenicity studies were conducted in Charles River CD-1 mice at doses of 5, 15, and 50 mg/kg/day and in Sprague-Dawley rats at doses of 1.5, 15, and 50 mg/kg/day (top doses equivalent to 10 and 20 times, respectively, the maximum recommended human dose of 24 mg/day on a mg/m2 basis). In the male rat, there was a significant increase in testicular Leydig cell adenomas at all doses tested, i.e., ≥1.5 mg/kg (0.6 times the maximum recommended human dose on a mg/m2 basis). This finding is of questionable significance because the endocrine mechanisms believed to be involved in the production of Leydig cell hyperplasia and adenomas in rats are not relevant to humans. In the female mouse, there was an increase in benign uterine endometrial polyps at a dose of 50 mg/kg/day (10 times the maximum recommended human dose on a mg/m2 basis).
Ropinirole was not mutagenic or clastogenic in the in vitro Ames test, the in vitro chromosome aberration test in human lymphocytes, the in vitro mouse lymphoma (L1578Y cells) assay, and the in vivo mouse micronucleus test.
When administered to female rats prior to and during mating and throughout pregnancy, ropinirole caused disruption of implantation at doses of 20 mg/kg/day (8 times the maximum recommended human dose on a mg/m2 basis) or greater. This effect is thought to be due to the prolactin-lowering effect of ropinirole. In humans, chorionic gonadotropin, not prolactin, is essential for implantation. In rat studies using low doses (5 mg/kg) during the prolactin-dependent phase of early pregnancy (gestation days 0 to 8), ropinirole did not affect female fertility at dosages up to 100 mg/kg/day (40 times the maximum recommended human dose on a mg/m2 basis). No effect on male fertility was observed in rats at dosages up to 125 mg/kg/day (50 times the maximum recommended human dose on a mg/m2 basis).

PREGNANCY

Pregnancy Category C.
In animal reproduction studies, ropinirole has been shown to have adverse effects on embryo-fetal development, including teratogenic effects. Ropinirole given to pregnant rats during organogenesis (20 mg/kg on gestation days 6 and 7 followed by 20, 60, 90, 120, or 150 mg/kg on gestation days 8 through 15) resulted in decreased fetal body weight at 60 mg/kg/day, increased fetal death at 90 mg/kg/day, and digital malformations at 150 mg/kg/day (24, 36, and 60 times the maximum recommended human dose on a mg/m2 basis, respectively). The combined administration of ropinirole (10 mg/kg/day, 8 times the maximum recommended human dose on a mg/m2 basis) and L-dopa (250 mg/kg/day) to pregnant rabbits during organogenesis produced a greater incidence and severity of fetal malformations (primarily digit defects) than were seen in the offspring of rabbits treated with L-dopa alone. No indication of an effect on development of the conceptus was observed in rabbits when a maternally toxic dose of ropinirole was administered alone (20 mg/kg/day, 16 times the maximum recommended human dose on a mg/m2 basis). In a perinatal-postnatal study in rats, 10 mg/kg/day (4 times the maximum recommended human dose on a mg/m2 basis) of ropinirole impaired growth and development of nursing offspring and altered neurological development of female offspring.
There are no adequate and well-controlled studies using Ropinirole Tablets in pregnant women. Ropinirole Tablets should be used during pregnancy only if the potential benefit outweighs the potential risk to the fetus.

NURSING MOTHERS

Ropinirole Tablets inhibit prolactin secretion in humans and could potentially inhibit lactation.
Studies in rats have shown that Ropinirole Tablets and/or its metabolite(s) is excreted in breast milk. It is not known whether this drug is excreted in human milk. Because many drugs are excreted in human milk and because of the potential for serious adverse reactions in nursing infants from Ropinirole Tablets, a decision should be made whether to discontinue nursing or to discontinue the drug, taking into account the importance of the drug to the mother.

PEDIATRIC USE

Safety and effectiveness in the pediatric population have not been established.

ADVERSE REACTIONS

Parkinson’s Disease
During the premarketing development of Ropinirole Tablets, patients received Ropinirole Tablets either without L-dopa (early Parkinson’s disease studies) or as concomitant therapy with L-dopa (advanced Parkinson’s disease studies). Because these 2 populations may have differential risks for various adverse events, this section will, in general, present adverse event data for these 2 populations separately.
Early Parkinson’s Disease (Without L-dopa)
The most commonly observed adverse events (>5%) in the double-blind, placebo-controlled early Parkinson’s disease trials associated with the use of Ropinirole Tablets (n = 157) not seen at an equivalent frequency among the placebo-treated patients (n = 147) were, in order of decreasing incidence: nausea, dizziness, somnolence, headache, vomiting, syncope, fatigue, dyspepsia, viral infection, constipation, pain, increased sweating, asthenia, dependent/leg edema, orthostatic symptoms, abdominal pain, pharyngitis, confusion, hallucinations, urinary tract infections, and abnormal vision.
Approximately 24% of 157 patients treated with Ropinirole Tablets who participated in the double-blind, placebo-controlled early Parkinson’s disease (without L-dopa) trials discontinued treatment due to adverse events compared to 13% of 147 patients who received placebo. The adverse events most commonly causing discontinuation of treatment by patients treated with Ropinirole Tablets were: nausea (6.4%), dizziness (3.8%), aggravated Parkinson’s disease (1.3%), hallucinations (1.3%), somnolence (1.3%), vomiting (1.3%), and headache (1.3%). Of these, hallucinations appear to be dose-related. While other adverse events leading to discontinuation may be dose-related, the titration design utilized in these trials precluded an adequate assessment of the dose response. For example, in the larger of the 2 trials described in CLINICAL PHARMACOLOGY: Clinical Trials, the difference in the rate of discontinuations emerged only after 10 weeks of treatment, suggesting, although not proving, that the effect could be related to dose.
Adverse Event Incidence in Controlled Clinical Studies
Table 2 lists treatment-emergent adverse events that occurred in ≥2% of patients with early Parkinson’s disease (without L-dopa) treated with Ropinirole Tablets participating in the double-blind, placebo-controlled studies and were numerically more common in the group treated with Ropinirole Tablets. In these studies, either Ropinirole Tablets or placebo was used as early therapy (i.e., without L-dopa).
The prescriber should be aware that these figures cannot be used to predict the incidence of adverse events in the course of usual medical practice where patient characteristics and other factors differ from those that prevailed in the clinical studies. Similarly, the cited frequencies cannot be compared with figures obtained from other clinical investigations involving different treatments, uses, and investigators. However, the cited figures do provide the prescribing physician with some basis for estimating the relative contribution of drug and non-drug factors to the adverse-events incidence rate in the population studied.
Table 2. Treatment-Emergent Adverse Event * Incidence in Double-Blind, Placebo-Controlled Early Parkinson’s Disease (Without L-dopa) Trials (Events ≥2% of Patients Treated With Ropinirole Tablets and Numerically More Frequent Than the Placebo Group)

Adverse Experience | Ropinirole Tablets (n = 157) (%) | Placebo (n = 147) (%)
Autonomic nervous system
Flushing | 3 | 1
Dry mouth | 5 | 3
Increased sweating | 6 | 4
Body as a whole
Asthenia | 6 | 1
Chest pain | 4 | 2
Dependent edema | 6 | 3
Leg edema | 7 | 1
Fatigue | 11 | 4
Malaise | 3 | 1
Pain | 8 | 4
Cardiovascular general
Hypertension | 5 | 3
Hypotension | 2 | 0
Orthostatic symptoms | 6 | 5
Syncope | 12 | 1
Central/peripheral nervous system
Dizziness | 40 | 22
Hyperkinesia | 2 | 1
Hypesthesia | 4 | 2
Vertigo | 2 | 0
Gastrointestinal system
Abdominal pain | 6 | 3
Anorexia | 4 | 1
Dyspepsia | 10 | 5
Flatulence | 3 | 1
Nausea | 60 | 22
Vomiting | 12 | 7
Heart rate/rhythm
Extrasystoles | 2 | 1
Atrial fibrillation | 2 | 0
Palpitation | 3 | 2
Tachycardia | 2 | 0
Metabolic/nutritional
Increased alkaline phosphatase | 3 | 1
Psychiatric
Amnesia | 3 | 1
Impaired concentration | 2 | 0
Confusion | 5 | 1
Hallucination | 5 | 1
Somnolence | 40 | 6
Yawning | 3 | 0
Reproductive male
Impotence | 3 | 1
Resistance mechanism
Viral infection | 11 | 3
Respiratory system
Bronchitis | 3 | 1
Dyspnea | 3 | 0
Pharyngitis | 6 | 4
Rhinitis | 4 | 3
Sinusitis | 4 | 3
Urinary system
Urinary tract infection | 5 | 4
Vascular extracardiac
Peripheral ischemia | 3 | 0
Vision
Eye abnormality | 3 | 1
Abnormal vision | 6 | 3
Xerophthalmia | 2 | 0

* Patients may have reported multiple adverse experiences during the study or at discontinuation; thus, patients may be included in more than one category.
Other events reported by 1% or more of early Parkinson’s disease (without L-dopa) patients treated with Ropinirole Tablets, but that were equally or more frequent in the placebo group, were: headache, upper respiratory infection, insomnia, arthralgia, tremor, back pain, anxiety, dyskinesias, aggravated Parkinsonism, depression, falls, myalgia, leg cramps, paresthesias, nervousness, diarrhea, arthritis, hot flushes, weight loss, rash, cough, hyperglycemia, muscle spasm, arthrosis, abnormal dreams, dystonia, increased salivation, bradycardia, gout, basal cell carcinoma, gingivitis, hematuria, and rigors.
Among the treatment-emergent adverse events in patients treated with Ropinirole Tablets, hallucinations appear to be dose-related.
The incidence of adverse events was not materially different between women and men.
Advanced Parkinson’s Disease (With L-dopa)
The most commonly observed adverse events (>5%), in the double-blind, placebo-controlled advanced Parkinson’s disease (with L-dopa) trials associated with the use of Ropinirole Tablets (n = 208) as an adjunct to L-dopa not seen at an equivalent frequency among the placebo-treated patients (n = 120) were, in order of decreasing incidence: dyskinesias, nausea, dizziness, aggravated Parkinsonism, somnolence, headache, insomnia, injury, hallucinations, falls, abdominal pain, upper respiratory infection, confusion, increased sweating, vomiting, viral infection, increased drug level, arthralgia, tremor, anxiety, urinary tract infection, constipation, dry mouth, pain, hypokinesia, and paresthesia.
Approximately 24% of 208 patients who received Ropinirole Tablets in the double-blind, placebo-controlled advanced Parkinson’s disease (with L-dopa) trials discontinued treatment due to adverse events compared to 18% of 120 patients who received placebo. The events most commonly (≥1%) causing discontinuation of treatment by patients treated with Ropinirole Tablets were: dizziness (2.9%), dyskinesias (2.4%), vomiting (2.4%), confusion (2.4%), nausea (1.9%), hallucinations (1.9%), anxiety (1.9%), and increased sweating (1.4%). Of these, hallucinations and dyskinesias appear to be dose-related.
Adverse Event Incidence in Controlled Clinical Studies
Table 3 lists treatment-emergent adverse events that occurred in ≥2% of patients with advanced Parkinson’s disease (with L-dopa) treated with Ropinirole Tablets who participated in the double-blind, placebo-controlled studies and were numerically more common in the group treated with Ropinirole Tablets. In these studies, either Ropinirole Tablets or placebo was used as an adjunct to L-dopa. Adverse events were usually mild or moderate in intensity.
The prescriber should be aware that these figures cannot be used to predict the incidence of adverse events in the course of usual medical practice where patient characteristics and other factors differ from those that prevailed in the clinical studies. Similarly, the cited frequencies cannot be compared with figures obtained from other clinical investigations involving different treatments, uses, and investigators. However, the cited figures do provide the prescribing physician with some basis for estimating the relative contribution of drug and non-drug factors to the adverse events incidence rate in the population studied.
Table 3. Treatment-Emergent Adverse Event* Incidence in Double-Blind, Placebo-Controlled Advanced Parkinson’s Disease (With L-dopa) Trials (Events ≥2% of Patients Treated With Ropinirole Tablets and Numerically More Frequent Than the Placebo Group)

Adverse Experience | Ropinirole Tablets (n = 208) (%) | Placebo (n = 120) (%)
Autonomic nervous system
Dry mouth | 5 | 1
Increased sweating | 7 | 2
Body as a whole
Increased drug level | 7 | 3
Pain | 5 | 3
Cardiovascular general
Hypotension | 2 | 1
Syncope | 3 | 2
Central/peripheral nervous system
Dizziness | 26 | 16
Dyskinesia | 34 | 13
Falls | 10 | 7
Headache | 17 | 12
Hypokinesia | 5 | 4
Paresis | 3 | 0
Paresthesia | 5 | 3
Tremor | 6 | 3
Gastrointestinal system
Abdominal pain | 9 | 8
Constipation | 6 | 3
Diarrhea | 5 | 3
Dysphagia | 2 | 1
Flatulence | 2 | 1
Nausea | 30 | 18
Increased saliva | 2 | 1
Vomiting | 7 | 4
Metabolic/nutritional
Weight decrease | 2 | 1
Musculoskeletal system
Arthralgia | 7 | 5
Arthritis | 3 | 1
Psychiatric
Amnesia | 5 | 1
Anxiety | 6 | 3
Confusion | 9 | 2
Abnormal dreaming | 3 | 2
Hallucinations | 10 | 4
Nervousness | 5 | 3
Somnolence | 20 | 8
Red blood cell
Anemia | 2 | 0
Resistance mechanism
Upper respiratory tract infection | 9 | 8
Respiratory system
Dyspnea | 3 | 2
Urinary system
Pyuria | 2 | 1
Urinary incontinence | 2 | 1
Urinary tract infection | 6 | 3
Vision
Diplopia | 2 | 1

* Patients may have reported multiple adverse experiences during the study or at discontinuation; thus, patients may be included in more than one category.
Other events reported by 1% or more of patients treated with both Ropinirole Tablets and L-dopa, but equally or more frequent in the placebo/L-dopa group, were: myocardial infarction, orthostatic symptoms, virus infections, asthenia, dyspepsia, myalgia, back pain, depression, leg cramps, fatigue, rhinitis, chest pain, hematuria, vertigo, tinnitus, leg edema, hot flushes, abnormal gait, hyperkinesia, and pharyngitis.
Among the treatment-emergent adverse events in patients treated with Ropinirole Tablets, hallucinations and dyskinesias appear to be dose-related.
Restless Legs Syndrome
The most commonly observed adverse events (>5%) in the 12-week double-blind, placebo-controlled trials in the treatment of Restless Legs Syndrome with Ropinirole Tablets (n = 496) and at least twice the rate for placebo-treated patients (n = 500) were, in order of decreasing incidence: nausea, somnolence, vomiting, dizziness, and fatigue (see Table 4). Occurrences of nausea in clinical trials were generally mild to moderate in intensity (see also DOSAGE AND ADMINISTRATION: General Dosing Considerations).
Approximately 5% of 496 patients treated with Ropinirole Tablets who participated in the double-blind, placebo-controlled trials in the treatment of RLS discontinued treatment due to adverse events compared to 4% of 500 patients who received placebo. The adverse events most commonly causing discontinuation of treatment by patients treated with Ropinirole Tablets were: nausea (1.6%), dizziness (0.8 %), and headache (0.8%).
Adverse Event Incidence in Controlled Clinical Studies
Table 4 lists treatment-emergent adverse events that occurred in ≥2% of patients with RLS treated with Ropinirole Tablets participating in the 12-week double-blind, placebo-controlled studies and were numerically more common in the group treated with Ropinirole Tablets.
The prescriber should be aware that these figures cannot be used to predict the incidence of adverse events in the course of usual medical practice where patient characteristics and other factors differ from those that prevailed in the clinical studies. Similarly, the cited frequencies cannot be compared with figures obtained from other clinical investigations involving different treatments, uses, and investigators. However, the cited figures do provide the prescribing physician with some basis for estimating the relative contribution of drug and non-drug factors to the adverse-events incidence rate in the population studied.
Table 4. Treatment-Emergent Adverse Event Incidence in Double-Blind, Placebo-Controlled RLS Trials (Events ≥2% of Patients Treated With Ropinirole Tablets and Numerically More Frequent Than the Placebo Group)

Adverse Experience | Ropinirole Tablets (n = 496) (%) | Placebo (n =500) (%)
Ear and labyrinth disorders
Vertigo | 2 | 1
Gastrointestinal disorders
Nausea | 40 | 8
Vomiting | 11 | 2
Diarrhea | 5 | 3
Dyspepsia | 4 | 3
Dry mouth | 3 | 2
Abdominal pain upper | 3 | 1
General disorders and administration site conditions
Fatigue | 8 | 4
Edema peripheral | 2 | 1
Infections and infestations
Nasopharyngitis | 9 | 8
Influenza | 3 | 2
Musculoskeletal and connective tissue disorders
Arthralgia | 4 | 3
Muscle cramps | 3 | 2
Pain in extremity | 3 | 2
Nervous system disorders
Somnolence | 12 | 6
Dizziness | 11 | 5
Paresthesia | 3 | 1
Respiratory, thoracic, and mediastinal disorders
Cough | 3 | 2
Nasal congestion | 2 | 1
Skin and subcutaneous tissue disorders
Hyperhidrosis | 3 | 1

Other events reported by 2% or more of patients treated with Ropinirole Tablets, but equally or more frequent in the placebo group, were headache, insomnia, restless legs syndrome, upper respiratory tract infection, back pain, and sinusitis.
Other Adverse Events Observed During All Phase 2/3 Clinical Trials for Parkinson’s Disease
Ropinirole Tablets have been administered to 1,599 individuals in clinical trials. During these trials, all adverse events were recorded by the clinical investigators using terminology of their own choosing. To provide a meaningful estimate of the proportion of individuals having adverse events, similar types of events were grouped into a smaller number of standardized categories using modified WHOART dictionary terminology. These categories are used in the listing below. The frequencies presented represent the proportion of the 1,599 individuals exposed to Ropinirole Tablets who experienced events of the type cited on at least 1 occasion while receiving Ropinirole Tablets. All reported events that occurred at least twice (or once for serious or potentially serious events), except those already listed above, trivial events, and terms too vague to be meaningful, are included without regard to determination of a causal relationship to Ropinirole Tablets, except that events very unlikely to be drug-related have been deleted.
Events are further classified within body system categories and enumerated in order of decreasing frequency using the following definitions: frequent adverse events are defined as those occurring in at least 1/100 patients and infrequent adverse events are those occurring in 1/100 to 1/1,000 patients and rare events are those occurring in fewer than 1/1,000 patients.
Body as a Whole
Infrequent: Cellulitis, peripheral edema, fever, influenza-like symptoms, enlarged abdomen, precordial chest pain, and generalized edema. Rare: Ascites.
Cardiovascular
Infrequent: Cardiac failure, bradycardia, tachycardia, supraventricular tachycardia, angina pectoris, bundle branch block, cardiac arrest, cardiomegaly, aneurysm, mitral insufficiency. Rare: Ventricular tachycardia.
Central/Peripheral Nervous System
Frequent: Neuralgia. Infrequent: Involuntary muscle contractions, hypertonia, dysphonia, abnormal coordination, extrapyramidal disorder, migraine, choreoathetosis, coma, stupor, aphasia, convulsions, hypotonia, peripheral neuropathy, paralysis. Rare: Grand mal convulsions, hemiparesis, hemiplegia.
Endocrine
Infrequent:Hypothyroidism, gynecomastia, hyperthyroidism. Rare: Goiter, SIADH.
Gastrointestinal
Infrequent: Increased hepatic enzymes, bilirubinemia, cholecystitis, cholelithiasis colitis, dysphagia, periodontitis, fecal incontinence, gastroesophageal reflux, hemorrhoids, toothache, eructation, gastritis, esophagitis, hiccups, diverticulitis, duodenal ulcer, gastric ulcer, melena, duodenitis, gastrointestinal hemorrhage, glossitis, rectal hemorrhage, pancreatitis, stomatitis and ulcerative stomatitis, tongue edema. Rare:Biliary pain, hemorrhagic gastritis, hematemesis, salivary duct obstruction.
Hematologic
Infrequent: Purpura, thrombocytopenia, hematoma, Vitamin B12 deficiency, hypochromic anemia, eosinophilia, leukocytosis, leukopenia, lymphocytosis, lymphopenia, lymphedema.
Metabolic/Nutritional
Frequent: Increased BUN. Infrequent: Hypoglycemia, increased alkaline phosphatase, increased LDH, weight increase, hyperphosphatemia, hyperuricemia, diabetes mellitus, glycosuria, hypokalemia, hypercholesterolemia, hyperkalemia, acidosis, hyponatremia, thirst, increased CPK, dehydration. Rare:Hypochloremia.
Musculoskeletal
Infrequent: Aggravated arthritis, tendonitis, osteoporosis, bursitis, polymyalgia rheumatica, muscle weakness, skeletal pain, torticollis. Rare: Dupuytren’s contracture requiring surgery.
Neoplasm
Infrequent:Malignant breast neoplasm. Rare: Bladder carcinoma, benign brain neoplasm, esophageal carcinoma, malignant laryngeal neoplasm, lipoma, rectal carcinoma, uterine neoplasm.
Psychiatric
Infrequent:Increased libido, agitation, apathy, impaired concentration, depersonalization, paranoid reaction, personality disorder, euphoria, delirium, dementia, delusion, emotional lability, decreased libido, manic reaction, somnambulism, aggressive reaction, neurosis. Rare: Suicide attempt.
Genitourinary
Infrequent: Amenorrhea, vaginal hemorrhage, penile disorder, prostatic disorder, balanoposthitis, epididymitis, perineal pain, dysuria, micturition frequency, albuminuria, nocturia, polyuria, renal calculus. Rare: Breast enlargement, mastitis, uterine hemorrhage, ejaculation disorder, Peyronie’s disease, pyelonephritis, acute renal failure, uremia.
Resistance Mechanism
Infrequent: Herpes zoster, otitis media, sepsis, abscess, herpes simplex, fungal infection, genital moniliasis.
Respiratory
Infrequent: Asthma, epistaxis, laryngitis, pleurisy, pulmonary edema.
Skin/Appendage
Infrequent:Pruritus, dermatitis, eczema, skin ulceration, alopecia, skin hypertrophy, skin discoloration, urticaria, fungal dermatitis, furunculosis, hyperkeratosis, photosensitivity reaction, psoriasis, maculopapular rash, psoriaform rash, seborrhea.
Special Senses
Infrequent: Tinnitus, earache, decreased hearing, abnormal lacrimation, conjunctivitis, blepharitis, glaucoma, abnormal accommodation, blepharospasm, eye pain, photophobia. Rare: Scotoma.
Vascular Extracardiac
Infrequent:Varicose veins, phlebitis, peripheral gangrene. Rare: Limb embolism, pulmonary embolism, gangrene, subarachnoid hemorrhage, deep thrombophlebitis, leg thrombophlebitis, thrombosis.
Falling Asleep During Activities of Daily Living
Patients treated with Ropinirole Tablets have reported falling asleep while engaged in activities of daily living, including operation of a motor vehicle which sometimes resulted in accidents (see bolded WARNING).
Other Adverse Events Observed During Phase 2/3 Clinical Trials for RLS
Ropinirole Tablets has been administered to 911 individuals in clinical trials. During these trials, all adverse events were recorded by the clinical investigators using terminology of their own choosing. To provide a meaningful estimate of the proportion of individuals having adverse events, similar types of events were grouped into a smaller number of standardized categories using MedDRA dictionary terminology. These categories are used in the listing below. The frequencies presented represent the proportion of the 911 individuals exposed to Ropinirole Tablets who experienced events of the type cited on at least one occasion while receiving Ropinirole Tablets. All reported events that occurred at least twice (or once for serious or potentially serious events), except those already listed, trivial events, and terms too vague to be meaningful, are included without regard to determination of a causal relationship to Ropinirole Tablets, except that events very unlikely to be drug-related have been deleted.
Events are further classified within body system categories and enumerated in order of decreasing frequency using the following definitions: frequent adverse events are defined as those occurring in at least 1/100 patients and infrequent adverse events are those occurring in 1/100 to 1/1,000 patients.
Blood and Lymphatic System Disorders
Infrequent: Anemia, lymphadenopathy.
Cardiac Disorders
Frequent: Palpitations. Infrequent: Acute coronary syndrome, angina pectoris, angina unstable, bradycardia, cardiac failure, cardiovascular disorder, coronary artery disease, myocardial infarction, sick sinus syndrome, tachycardia.
Congenital, Familial, and Genetic Disorders
Infrequent: Pigmented nevus.
Ear and Labyrinth Disorders
Infrequent: Ear pain, middle ear effusion, tinnitus.
Endocrine Disorders
Infrequent: Goiter, hypothyroidism.
Eye Disorders
Infrequent: Blepharitis, conjunctival hemorrhage, conjunctivitis, eye irritation, eye pain, keratoconjunctivitis sicca, vision blurred, visual acuity reduced, visual disturbance.
Gastrointestinal Disorders
Frequent: Abdominal pain, constipation, gastroesophageal reflux disease, stomach discomfort, toothache. Infrequent: Abdominal adhesions, abdominal discomfort, abdominal distension, abdominal pain lower, duodenal ulcer, dysphagia, eructation, flatulence, gastric disorder, gastric hemorrhage, gastric polyps, gastric ulcer, gastritis, gastrointestinal pain, hematemesis, hemorrhoids, hiatus hernia, intestinal obstruction, irritable bowel syndrome, loose stools, mouth ulceration, pancreatitis acute, peptic ulcer, rectal hemorrhage, reflux esophagitis.
General Disorders and Administration Site Conditions
Frequent: Asthenia, chest pain, influenza-like illness, rigors.Infrequent: Chest discomfort, feeling cold, feeling hot, hunger, lethargy, malaise, edema, pain, pyrexia.
Hepatobiliary Disorders
Infrequent: Cholecystitis, cholelithiasis, ischemic hepatitis.
Immune System Disorders
Infrequent: Hypersensitivity.
Infections and Infestations
Frequent:Bronchitis, gastroenteritis, gastroenteritis viral, lower respiratory tract infection, rhinitis, tooth abscess, urinary tract infection. Infrequent: Appendicitis, bacterial infection, bladder infection, bronchitis acute, candidiasis, cellulitis, cystitis, diarrhea infectious, diverticulitis, ear infection, folliculitis, fungal infection, gastrointestinal infection, herpes simplex, infected cyst, laryngitis, localized infection, mastitis, otitis externa, otitis media, pharyngitis, pneumonia, postoperative infection, respiratory tract infection, tonsillitis, tooth infection, vaginal candidiasis, vaginal infection, vaginal mycosis, viral infection, viral upper respiratory tract infection, wound infection.
Injury, Poisoning, and Procedural Complications
Infrequent: Concussion, lower limb fracture, post procedural hemorrhage, road traffic accident.
Investigations
Infrequent: Blood cholesterol increased, blood iron decreased, blood pressure increased, blood urine present, hemoglobin decreased, heart rate increased, protein urine present, weight decreased, weight increased.
Metabolism and Nutrition Disorders
Infrequent: Anorexia, decreased appetite, diabetes mellitus non-insulin-dependent, fluid retention, gout, hypercholesterolemia.
Musculoskeletal and Connective Tissue Disorders
Frequent: Muscle spasms, musculoskeletal stiffness, myalgia, neck pain, osteoarthritis, tendonitis. Infrequent: Arthritis, aseptic necrosis bone, bone pain, bone spur, bursitis, groin pain, intervertebral disc degeneration, intervertebral disc protrusion, joint stiffness, joint swelling, localized osteoarthritis, monoarthritis, muscle contracture, muscle tightness, muscle twitching, osteoporosis, rotator cuff syndrome, sacroiliitis, synovitis.
Neoplasms Benign, Malignant, and Unspecified
Infrequent: Anaplastic thyroid cancer, angiomyolipoma, basal cell carcinoma, breast cancer, gastric cancer, gastrointestinal stromal tumor, malignant melanoma, prostate cancer, skin papilloma, squamous cell carcinoma, uterine leiomyoma.
Nervous System Disorders
Frequent: Hypoesthesia, migraine. Infrequent: Amnesia, aphasia, ataxia, balance disorder, benign intracranial hypertension, burning sensation, carpal tunnel syndrome, disturbance in attention, dizziness postural, dysgeusia, dyskinesia, head discomfort, hyperesthesia, hypersomnia, lethargy, loss of consciousness, memory impairment, migraine with aura, migraine without aura, neuralgia, sciatica, sedation, sinus headache, sleep apnea syndrome, syncope vasovagal, tension headache, transient ischemic attack, tremor.
Psychiatric Disorders
Frequent: Anxiety, depression, irritability, sleep disorder. Infrequent: Abnormal dreams, agitation, bruxism, confusional state, depressed mood, disorientation, early morning awakening, libido decreased, loss of libido, mood swings, nervousness, nightmare, panic attack, stress symptoms, tension.
Renal and Urinary Disorders
Infrequent: Dysuria, hematuria, hypertonic bladder, micturition disorder, nephrolithiasis, nocturia, pollakiuria, proteinuria, urinary retention.
Reproductive System and Breast Disorders
Frequent:Erectile dysfunction. Infrequent: Breast cyst, dysmenorrhea, menorrhagia, pelvic peritoneal adhesions, postmenopausal hemorrhage, premenstrual syndrome, prostatitis.
Respiratory, Thoracic and Mediastinal Disorders
Frequent:Asthma, pharyngolaryngeal pain. Infrequent: Dry throat, dyspnea, epistaxis, hemoptysis, hoarseness, interstitial lung disease, nasal mucosal disorder, nasal polyps, respiratory tract congestion, rhinorrhea, sinus congestion, sneezing, wheezing, yawning.
Skin and Subcutaneous Tissue Disorders
Frequent: Night sweats, rash. Infrequent: Acne, actinic keratosis, alopecia, cold sweat, dermatitis, dermatitis allergic, dermatitis contact, eczema, exanthem, face edema, photosensitivity reaction, pruritus, psoriasis, rash pruritic, skin lesion, urticaria.
Vascular Disorders
Frequent:Hot flush, hypertension, hypotension. Infrequent: Atherosclerosis, circulatory collapse, flushing, hematoma, thrombosis, varicose vein.
Postmarketing Reports
Psychiatric Disorders:Impulse control symptoms, pathological gambling, increased libido including hypersexuality.

DRUG ABUSE AND DEPENDENCE

CONTROLLED SUBSTANCE

Ropinirole Hydrochloride is not a controlled substance.
Physical and Psychological Dependence
Animal studies and human clinical trials with Ropinirole Tablets did not reveal any potential for drug-seeking behavior or physical dependence.

OVERDOSAGE

In the Parkinson's disease program, there have been patients who accidentally or intentionally took more than their prescribed dose of ropinirole. The largest overdose reported in the Parkinson's disease clinical trials was 435 mg taken over a 7-day period (62.1 mg/day). Of patients who received a dose greater than 24 mg/day, reported symptoms included adverse events commonly reported during dopaminergic therapy (nausea, dizziness), as well as visual hallucinations, hyperhidrosis, claustrophobia, chorea, palpitations, asthenia, and nightmares. Additional symptoms reported for doses of 24 mg or less or for overdoses of unknown amount included vomiting, increased coughing, fatigue, syncope, vasovagal syncope, dyskinesia, agitation, chest pain, orthostatic hypotension, somnolence, and confusional state.

Overdose Management
It is anticipated that the symptoms of overdose with Ropinirole Tablets will be related to its dopaminergic activity. General supportive measures are recommended. Vital signs should be maintained, if necessary. Removal of any unabsorbed material (e.g., by gastric lavage) should be considered.

DOSAGE & ADMINISTRATION

General Dosing Considerations for Parkinson's Disease and RLS
Ropinirole Tablets can be taken with or without food. Patients may be advised that taking Ropinirole Tablets with food may reduce the occurrence of nausea. However, this has not been established in controlled clinical trials.
If a significant interruption in therapy with Ropinirole Tablets has occurred, retitration of therapy may be warranted.
Geriatric Use
Pharmacokinetic studies demonstrated a reduced clearance of ropinirole in the elderly (see CLINICAL PHARMACOLOGY). Dose adjustment is not necessary since the dose is individually titrated to clinical response.
Renal Impairment
The pharmacokinetics of ropinirole were not altered in patients with moderate renal impairment (see CLINICAL PHARMACOLOGY). Therefore, no dosage adjustment is necessary in patients with moderate renal impairment. The use of Ropinirole Tablets in patients with severe renal impairment has not been studied.
Hepatic Impairment
The pharmacokinetics of ropinirole have not been studied in patients with hepatic impairment. Since patients with hepatic impairment may have higher plasma levels and lower clearance, Ropinirole Tablets should be titrated with caution in these patients.
Dosing for Parkinson’s Disease
In all clinical studies, dosage was initiated at a subtherapeutic level and gradually titrated to therapeutic response. The dosage should be increased to achieve a maximum therapeutic effect, balanced against the principal side effects of nausea, dizziness, somnolence, and dyskinesia.
The recommended starting dose for Parkinson’s disease is 0.25 mg 3 times daily. Based on individual patient response, dosage should then be titrated with weekly increments as described in Table 5. After week 4, if necessary, daily dosage may be increased by 1.5 mg/day on a weekly basis up to a dose of 9 mg/day, and then by up to 3 mg/day weekly to a total dose of 24 mg/day. Doses greater than 24 mg/day have not been tested in clinical trials.
Table 5. Ascending-Dose Schedule of Ropinirole Tablets for Parkinson’s Disease

Week | Dosage | Total Daily Dose
1 | 0.25 mg 3 times daily | 0.75 mg
2 | 0.5 mg 3 times daily | 1.5 mg
3 | 0.75 mg 3 times daily | 2.25 mg
4 | 1 mg 3 times daily | 3 mg

When Ropinirole Tablets are administered as adjunct therapy to L-dopa, the concurrent dose of L-dopa may be decreased gradually as tolerated. L-dopa dosage reduction was allowed during the advanced Parkinson’s disease (with L-dopa) study if dyskinesias or other dopaminergic effects occurred. Overall, reduction of L-dopa dose was sustained in 87% of patients treated with Ropinirole Tablets and in 57% of patients on placebo. On average the L-dopa dose was reduced by 31% in patients treated with Ropinirole Tablets.
Ropinirole Tablets for Parkinson’s disease patients should be discontinued gradually over a 7-day period. The frequency of administration should be reduced from 3 times daily to twice daily for 4 days. For the remaining 3 days, the frequency should be reduced to once daily prior to complete withdrawal of Ropinirole Tablets.
Dosing for Restless Legs Syndrome
In all clinical trials, the dose for Ropinirole Tablets was initiated at 0.25 mg once daily, 1 to 3 hours before bedtime. Patients were titrated based on clinical response and tolerability.
The recommended adult starting dosage for RLS is 0.25 mg once daily, 1 to 3 hours before bedtime. After 2 days, the dosage can be increased to 0.5 mg once daily and to 1 mg once daily at the end of the first week of dosing, then as shown in Table 6 as needed to achieve efficacy. For RLS, the safety and effectiveness of doses greater than 4 mg once daily have not been established.
Table 6. Dose Titration Schedule for RLS

Day/Week | Dosage to be taken once daily, 1 to 3 hours before bedtime
Days 1 and 2 | 0.25 mg
Days 3-7 | 0.5 mg
Week 2 | 1 mg
Week 3 | 1.5 mg
Week 4 | 2 mg
Week 5 | 2.5 mg
Week 6 | 3 mg
Week 7 | 4 mg

In clinical trials of patients being treated for RLS with doses up to 4 mg once daily, Ropinirole Tablets were discontinued without a taper.

HOW SUPPLIED

Tablets
Each circular, biconvex, film-coated tablet contains ropinirole as follows:
0.25 mg: white tablets debossed with “H” on one side and “121” on other side

NDC 46708-030-31 bottle of 100 tablets

0.5 mg: yellow tablets debossed with “H” on one side and “122” on other side

NDC 46708-031-31 bottle of 100 tablets

1 mg: green tablets debossed with “H” on one side and “123” on other side

NDC 46708-032-31 bottle of 100 tablets

2 mg: Peach tablets debossed with “H” on one side and “124” on other side

NDC 46708-033-31 bottle of 100 tablets

3 mg: Purple tablets debossed with “H” on one side and “125” on other side

NDC 46708-034-31 bottle of 100 tablets

4 mg: Pale brown tablets debossed with “H” on one side and “126” on other side

NDC 46708-035-31 bottle of 100 tablets

5 mg: Blue tablets debossed with “H” on one side and “127” on other side

NDC 46708-036-31 bottle of 100 tablets

STORAGE: Protect from light and moisture. Close container tightly after each use. Store at controlled room temperature 20°-25°C (68°-77°F) [see USP].
Alembic Pharmaceuticals Limited
Manufactured in India

Revision Date: 08/2024

SPL PATIENT PACKAGE INSERT

PHARMACIST DETACH HERE AND GIVE INSTRUCTIONS TO PATIENT
PATIENT INFORMATION
Ropinirole Tablets USP
If you have Restless Legs Syndrome (RLS, also known as Ekbom Syndrome), read this side
Read this information completely before you start taking Ropinirole Tablets.Read the information each time you get more medicine. There may be new information. This leaflet provides a summary about Ropinirole Tablets. It does not include everything there is to know about your medicine. This information should not take the place of discussions with your doctor about your medical condition or Ropinirole Tablets.
What is Ropinirole Tablets?
Ropinirole Tablets is a prescription medicine to treat moderate-to-severe primary Restless Legs Syndrome. It is sometimes used to treat Parkinson's disease. Having one of these conditions does not mean you have or will develop the other.
What is the most important information I should know about Ropinirole Tablets?

- Patients with RLS should take Ropinirole Tablets differently than patients with Parkinson's disease (see How should I take Ropinirole Tablets for RLS?for the recommended dosing for RLS). A lower dose of Ropinirole Tablets is generally needed for patients with RLS, and is taken once daily before bedtime.
- There are known side effects of Ropinirole Tablets. If you fall asleep or feel very sleepy while doing normal activities such as driving, faint, feel dizzy, nauseated, or sweaty when you stand up from sitting or lying down, you should talk with your doctor (see What are the possible side effects of Ropinirole Tablets?).
- Before starting Ropinirole Tablets, be sure to tell your doctor if you are taking any medicines that make you drowsy.

Who should not take Ropinirole Tablets?
You should not take Ropinirole Tablets if you are allergic to the active ingredient ropinirole or to any of the inactive ingredients. Your doctor and pharmacist have a list of the inactive ingredients.
What should I tell my doctor?
Be sure to tell your doctor if:

- you are pregnant or plan to become pregnant.
- you are breast-feeding.
- you have daytime sleepiness from a sleep disorder other than RLS or have unexpected sleepiness or periods of sleep while taking Ropinirole Tablets.
- you are taking any other prescription or over-the-counter medicines. Some of these medicines may increase your chances of getting side effects while taking Ropinirole Tablets.
- you start or stop taking other medicines while you are taking Ropinirole Tablets. This may increase your chances of getting side effects.
- you start or stop smoking while you are taking Ropinirole Tablets. Smoking may decrease the treatment effect of Ropinirole Tablets.
- you feel dizzy, nauseated, sweaty, or faint when you stand up from sitting or lying down.
- you drink alcoholic beverages. This may increase your chances of becoming drowsy or sleepy while taking Ropinirole Tablets.

How should I take Ropinirole Tablets for RLS?

- Be sure to take Ropinirole Tablets exactly as directed by your doctor or healthcare provider.
- The usual way to take Ropinirole Tablets is once in the evening, 1 to 3 hours before bedtime.
- Your doctor will start you on a low dose of Ropinirole Tablets. Your doctor may change the dose until you are taking the amount of medicine that is right for you to control your symptoms.
- If you miss your dose, do not double your next dose . Take only your usual dose 1 to 3 hours before your next bedtime.
- Contact your doctor, if you stop taking Ropinirole Tablets for any reason. Do not restart without consulting your doctor.
- You can take Ropinirole Tablets with or without food. Taking Ropinirole Tablets with food may decrease the chances of feeling nauseated.

What are the possible side effects of Ropinirole Tablets?

- Most people who take Ropinirole Tablets tolerate it well. The most commonly reported side effects in people taking Ropinirole Tablets for RLS are nausea, vomiting, dizziness, and drowsiness or sleepiness. You should be careful until you know if Ropinirole Tablets affects your ability to remain alert while doing normal daily activities, and you should watch for the development of significant daytime sleepiness or episodes of falling asleep. It is possible that you could fall asleep while doing normal activities such as driving a car, doing physical tasks, or using hazardous machinery while taking Ropinirole Tablets. Your chances of falling asleep while doing normal activities while taking Ropinirole Tablets are greater if you are taking other medicines that cause drowsiness.
- When you start taking Ropinirole Tablets or when you increase your dose, you may feel dizzy, nauseated, sweaty or faint, when first standing up from sitting or lying down. Therefore, do not stand up quickly after sitting or lying down, particularly if you have been sitting or lying down for a long period of time. Take a minute sitting on the edge of the bed or chair before you get up.
- Some patients taking ropinirole have shown urges to behave in a way unusual for them. Examples of this are an unusual urge to gamble or increased sexual urges and/or behaviors. If you or your family notices that you are developing any unusual behaviors, talk to your doctor.
- Hallucinations (unreal sounds, visions, or sensations) have been reported in patients taking Ropinirole Tablets. These were uncommon in patients taking Ropinirole Tablets for RLS. The risk is greater in patients with Parkinson's disease who are elderly, taking Ropinirole Tablets with L-dopa, or taking higher doses of Ropinirole Tablets than recommended for RLS.

This is not a complete list of side effects and should not take the place of discussions with your healthcare providers. Your doctor or pharmacist can give you a more complete list of possible side effects. Talk to your doctor about any side effects or problems you may have.
Call your doctor for medical advice about side effects. You may report side effects to FDA at 1-800-FDA-1088.
Other Information about Ropinirole Tablets

- Studies of people with Parkinson’s disease show that they may be at an increased risk of developing melanoma, a form of skin cancer, when compared to people without Parkinson’s disease. It is not known if this problem is associated with Parkinson’s disease or the medicines used to treat Parkinson’s disease. Ropinirole Tablets is one of the medicines used to treat Parkinson’s disease, therefore, patients being treated with Ropinirole Tablets should have periodic skin examinations.
- Take Ropinirole Tablets exactly as your doctor prescribes it.
- Do not share Ropinirole Tablets with other people, even if they have the same symptoms you have.
- Keep Ropinirole Tablets out of the reach of children.
- Store Ropinirole Tablets at room temperature out of direct sunlight.
- Keep Ropinirole Tablets in a tightly closed container.

This leaflet summarizes important information about Ropinirole Tablets. Medicines are sometimes prescribed for purposes other than those listed in this leaflet. Do not take Ropinirole Tablets for a condition for which it was not prescribed. For more information, talk with your doctor or pharmacist. They can give you information about Ropinirole Tablets that is written for healthcare professionals.
Alembic Pharmaceuticals Limited
Manufactured in India

Revision Date: 08/2024

PATIENT INFORMATION
Ropinirole Tablets USP
If you have Parkinson's desease, read this side
Read this information completely before you start taking Ropinirole Tablets. Read the information each time you get more medicine. There may be new information. This leaflet provides a summary about Ropinirole Tablets. It does not include everything there is to know about your medicine. This information should not take the place of discussions with your doctor about your medical condition or Ropinirole Tablets.
What is Ropinirole Tablets?
Ropinirole Tablets is a prescription medicine used to treat Parkinson's disease. It is also used to treat moderate-to-severe primary Restless Legs Syndrome. Having one of these conditions does not mean you have or will develop the other.
What is the most important information I should know about Ropinirole Tablets?

- Patients with Parkinson's disease should take Ropinirole Tablets differently than patients with Restless Legs Syndrome (see How should I take Ropinirole Tablets for Parkinson's disease?). For Parkinson's disease, a higher dose of Ropinirole Tablets is generally needed, and is taken more frequently throughout the day.
- There are known side effects of Ropinirole Tablets (see What are the possible side effects of Ropinirole Tablets?).
- If you fall asleep or feel very sleepy while doing normal activities such as driving, faint, feel dizzy, nauseated, or sweaty when you stand up from sitting or lying down, you should talk with your doctor.
- Hallucinations (unreal visions, sounds, or sensations) have been reported in patients taking Ropinirole Tablets. The risk is greater in patients with Parkinson's disease who are elderly, taking Ropinirole Tablets with L-dopa or taking higher doses of Ropinirole Tablets. If these occur, you should discuss them with your doctor.
- Ropinirole Tablets may make some of the side effects of L-dopa worse. Ropinirole Tablets may cause uncontrolled sudden movements or make such movements you already have worse or more frequent. You should notify your doctor in such a case as dosage adjustments to your anti-Parkinson’s medications may be necessary.
- Before starting Ropinirole Tablets, be sure to tell your doctor if you are taking any medicines that make you drowsy.

Who should not take Ropinirole Tablets?
You should not take Ropinirole Tablets if you are allergic to the active ingredient ropinirole or to any of the inactive ingredients. Your doctor and pharmacist have a list of the inactive ingredients.
What should I tell my doctor?
Be sure to tell your doctor if:

- you are pregnant or plan to become pregnant.
- you are breast-feeding.
- you have daytime sleepiness from a sleep disorder or have unexpected sleepiness or periods of sleep while taking Ropinirole Tablets.
- you are taking any other prescription or over-the-counter medicines. Some of these medicines may increase your chances of getting side effects while taking Ropinirole Tablets.
- you start or stop taking other medicines while you are taking Ropinirole Tablets. This may increase your chances of getting side effects.
- you start or stop smoking while you are taking Ropinirole Tablets. Smoking may decrease the treatment effect of Ropinirole Tablets.
- you feel dizzy, nauseated, sweaty, or faint when you first stand up from sitting or lying down.
- you drink alcoholic beverages. This may increase your chances of becoming drowsy or sleepy while taking Ropinirole Tablets.

How should I take Ropinirole Tablets for Parkinson's disease?

- Be sure to take your Ropinirole Tablets exactly as directed by your doctor or healthcare provider.
- Three times a day is the usual way to take Ropinirole Tablets for Parkinson's disease.
- Your doctor will start you on a low dose of Ropinirole Tablets. Your doctor will change the dose until you are taking the right amount of medicine to control your symptoms. It may take several weeks before you reach a dose that controls your symptoms.
- If you miss a dose, do not double your next dose.
- Contact your doctor, if you stop taking Ropinirole Tablets for any reason. Do not restart without consulting your doctor.
- Your doctor may prescribe Ropinirole Tablets alone or add Ropinirole Tablets to medicine that you are already taking for Parkinson's disease.
- You can take Ropinirole Tablets with or without food. Taking Ropinirole Tablets with food may decrease the chances of feeling nauseated.

What are the possible side effects of Ropinirole Tablets?

- Most people who take Ropinirole Tablets tolerate it well. The most commonly reported side effects in people taking Ropinirole Tablets are nausea, headache, dizziness, drowsiness or sleepiness.
- You should be careful until you know if Ropinirole Tablets affects your ability to remain alert while doing normal daily activities, and you should watch for the development of significant daytime sleepiness or episodes of falling asleep. It is possible that you could fall asleep while doing normal activities such as driving a car, doing physical tasks, or using hazardous machinery while taking Ropinirole Tablets. Your chances of falling asleep while doing normal activities while taking Ropinirole Tablets are greater if you are taking other medicines that cause drowsiness.
- When you start taking Ropinirole Tablets or when you increase your dose, you may feel dizzy, nauseated, sweaty or faint, when first standing up from sitting or lying down. Therefore, do not stand up quickly after sitting or lying down, particularly if you have been sitting or lying down for a long period of time. Take a minute sitting on the edge of the bed or chair before you get up.
- Some patients taking ropinirole have shown urges to behave in a way unusual for them. Examples of this are an unusual urge to gamble or increased sexual urges and/or behaviors. If you or your family notices that you are developing any unusual behaviors, talk to your doctor.
- Hallucinations (unreal visions, sounds, or sensations) have been reported in patients taking Ropinirole Tablets. The risk is greater in patients with Parkinson's disease who are elderly, taking Ropinirole Tablets with L-dopa, or taking higher amounts of Ropinirole Tablets.
- If you are taking L-dopa for Parkinson's disease, Ropinirole Tablets may make some of the side effects of L-dopa worse. Ropinirole Tablets may cause uncontrolled sudden movements or make such movements you already have worse or more frequent.

This is not a complete list of side effects and should not take the place of discussions with your healthcare providers. Your doctor or pharmacist can give you a more complete list of possible side effects. Talk to your doctor about any side effects or problems you may have.
Call your doctor for medical advice about side effects. You may report side effects to FDA at 1-800-FDA-1088.
Other Information about Ropinirole Tablets

- Studies of people with Parkinson’s disease show that they may be at an increased risk of developing melanoma, a form of skin cancer, when compared to people without Parkinson’s disease. It is not known if this problem is associated with Parkinson’s disease or the medicines used to treat Parkinson’s disease. Therefore, patients being treated with Ropinirole Tablets should have periodic skin examinations.
- Take Ropinirole Tablets exactly as your doctor prescribes it.
- Do not share Ropinirole Tablets with other people, even if they have the same symptoms you have.
- Keep Ropinirole Tablets out of the reach of children.
- Store Ropinirole Tablets at room temperature out of direct sunlight.
- Keep Ropinirole Tablets in a tightly closed container.

This leaflet summarizes important information about Ropinirole Tablets. Medicines are sometimes prescribed for purposes other than those listed in this leaflet. Do not take Ropinirole Tablets for a condition for which it was not prescribed. For more information, talk with your doctor or pharmacist. They can give you information about Ropinirole Tablets that is written for healthcare professionals.
Alembic Pharmaceuticals Limited
Manufactured in India

Revision Date: 08/2024

PACKAGE LABEL.PRINCIPAL DISPLAY PANEL - 0.25 mg

Ropinirole Tablets USP 0.25 mg (100 tablets in HDPE bottle)
Each film-coated tablet contains ropinirole hydrochloride USP equivalent to ropinirole free base..... 0.25 mg
46708-030-31

PACKAGE LABEL.PRINCIPAL DISPLAY PANEL - 0.5 mg

Ropinirole Tablets USP 0.5 mg (100 tablets in HDPE bottle)
Each film-coated tablet contains ropinirole hydrochloride USP equivalent to ropinirole free base..... 0.5 mg
46708-031-31

PACKAGE LABEL.PRINCIPAL DISPLAY PANEL - 1 mg

Ropinirole Tablets USP 1 mg (100 tablets in HDPE bottle)
Each film-coated tablet contains ropinirole hydrochloride USP equivalent to ropinirole free base..... 1 mg
46708-032-31

PACKAGE LABEL.PRINCIPAL DISPLAY PANEL - 2 mg

Ropinirole Tablets USP 2 mg (100 tablets in HDPE bottle)
Each film-coated tablet contains ropinirole hydrochloride USP equivalent to ropinirole free base..... 2 mg
46708-033-31

PACKAGE LABEL.PRINCIPAL DISPLAY PANEL - 3 mg

Ropinirole Tablets USP 3 mg (100 tablets in HDPE bottle)
Each film-coated tablet contains ropinirole hydrochloride USP equivalent to ropinirole free base..... 3 mg
46708-034-31

PACKAGE LABEL.PRINCIPAL DISPLAY PANEL - 4 mg

Ropinirole Tablets USP 4 mg (100 tablets in HDPE bottle)
Each film-coated tablet contains ropinirole hydrochloride USP equivalent to ropinirole free base..... 4 mg
46708-035-31

PACKAGE LABEL.PRINCIPAL DISPLAY PANEL - 5 mg

Ropinirole Tablets USP 5 mg (100 tablets in HDPE bottle)
Each film-coated tablet contains ropinirole hydrochloride USP equivalent to ropinirole free base..... 5 mg
46708-036-31